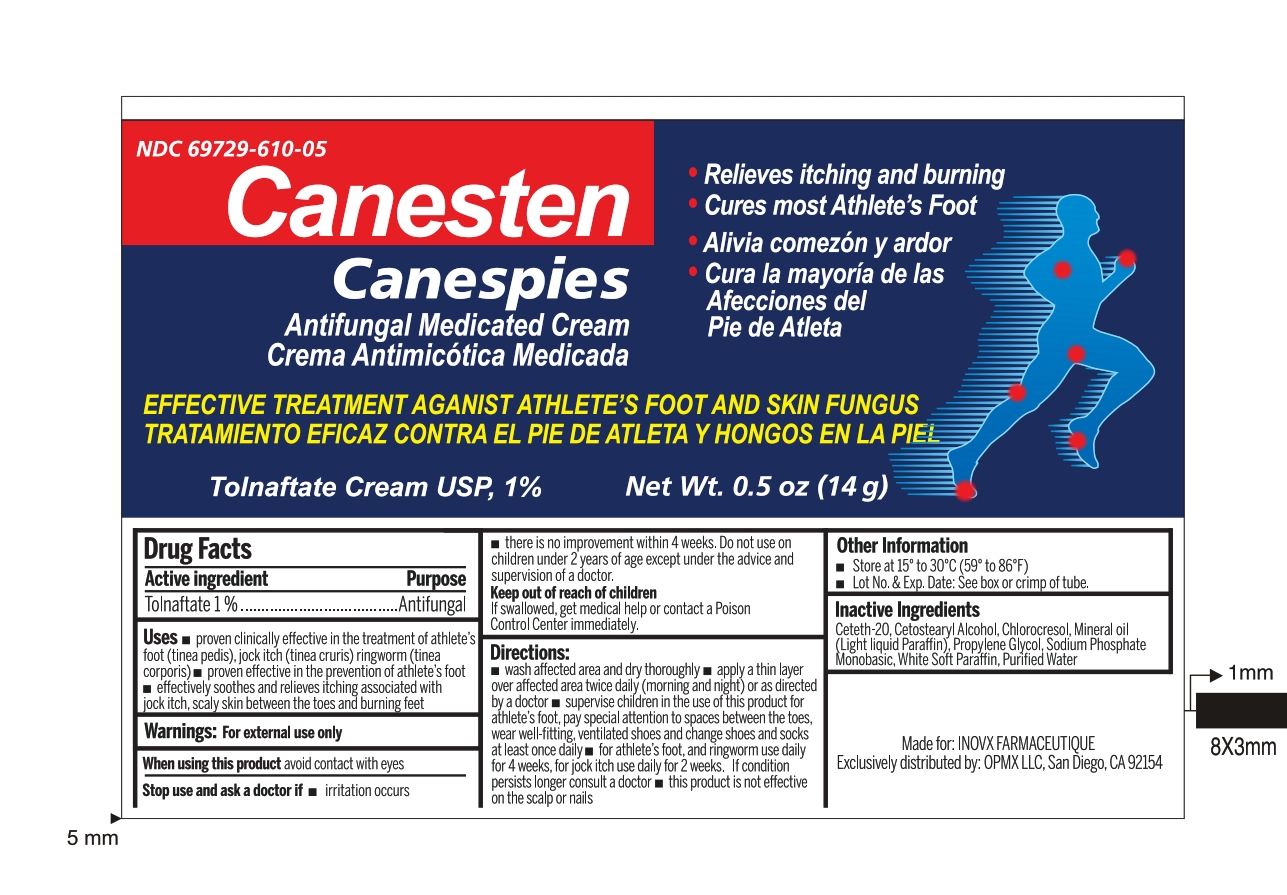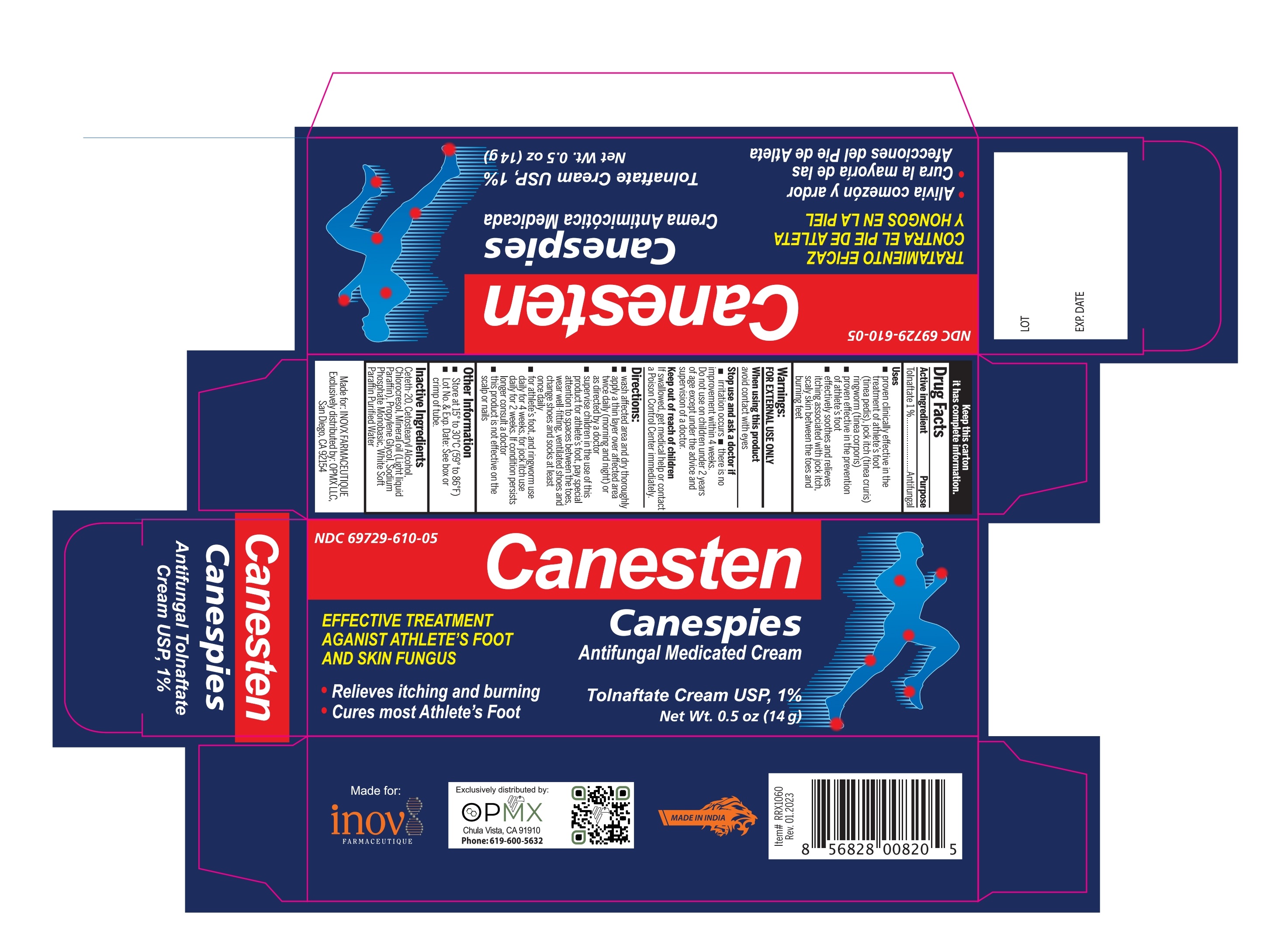 DRUG LABEL: CANESPIES
NDC: 69729-610 | Form: CREAM
Manufacturer: OPMX LLC
Category: otc | Type: HUMAN OTC DRUG LABEL
Date: 20240517

ACTIVE INGREDIENTS: TOLNAFTATE 1 g/100 g
INACTIVE INGREDIENTS: CETOSTEARYL ALCOHOL; MINERAL OIL; PARAFFIN; CETETH-20; PROPYLENE GLYCOL; WATER; SODIUM PHOSPHATE, MONOBASIC, UNSPECIFIED FORM; CHLOROCRESOL

ACTIVE INGREDIENTS

TOLNAFTATE 1%

PURPOSE

ANTIFUNGAL

USES

- PROVEN CLINICALLY EFFECTIVE IN THE TREATMENT OF ATHLETE'S FOOT (TINEA PEDIS), JOCK ITCH (TINEA CRURIS), RINGWORM (TINEA CORPORIS)
- PROVEN EFFECTIVE IN THE PREVENTION OF ATHLETE'S FOOT
- EFFECTIVELY SOOTHES AND RELIEVES ITCHING ASSOCIATED WITH JOCK ITCH, SCALY SKIN BETWEEN THE TOES AND BURNING FEET

WARNINGS

For external use only.

STOP USE AND ASK A DOCTOR IF

IRRITATION OCCURS
THERE IS NO IMPROVEMENT WITHIN 4 WEEKS.

DO NOT USE ON CHILDREN UNDER 2 YEARS OF AGE EXCEPT UNDER THE ADVICE AND SUPERVISION OF A DOCTOR.

WHEN USING THIS PRODUCT AVOID CONTACT WITH EYES.

Keep out of reach of children

- If swallowed get medical help or contact Poison Control Center right away.

DIRECTIONS

- WASH AFFECTED AREA AND DRY THOROUGHLY
- APPLY A THIN LAYER OVER AFFECTED AREA TWICE DAILY (MORNING AND NIGHT) OR AS DIRECTED BY A DOCTOR
- SUPERVISE CHILDREN IN THE USE OF THIS PRODUCT FOR ATHLETE'S FOOT, PAY SPECIAL ATTENTION TO SPACES BETWEEN THE TOES, WEAR WELL-FITTING, VENTILLATED SHOES AND CHANGE SHOES AND SOCKS AT LEAST ONCE DAILY
- FOR ATHLETE'S FOOT, AND RINGWORM USE DAILY FOR 4 WEEKS, FOR JOCK ITCH USE DAILY FOR 2 WEKS. IF CONDITION PERSISTS LONGER CONSULT A DOCTOR
- THIS PRODUCT IS NOT EFFECTIVE ON THE SCALP OR NAILS

OTHER INFORMATION

- STORE AT 15° TO 30°C (59°F TO 86°F)
- LOT NO. & EXP. DATE: SEE BOX OR CRIMP OF TUBE

INACTIVE INGREDIENTS

CETETH-20, CETYL ALCOHOL, CHLOROCRESOL, MINERAL OIL, PROPYLENE GLYCOL, SODIUM PHOSPHATE MONOBASIC, WHITE SOFT PARAFFIN, PURIFIED WATER

PACKAGE LABEL

NDC 69729-610-05